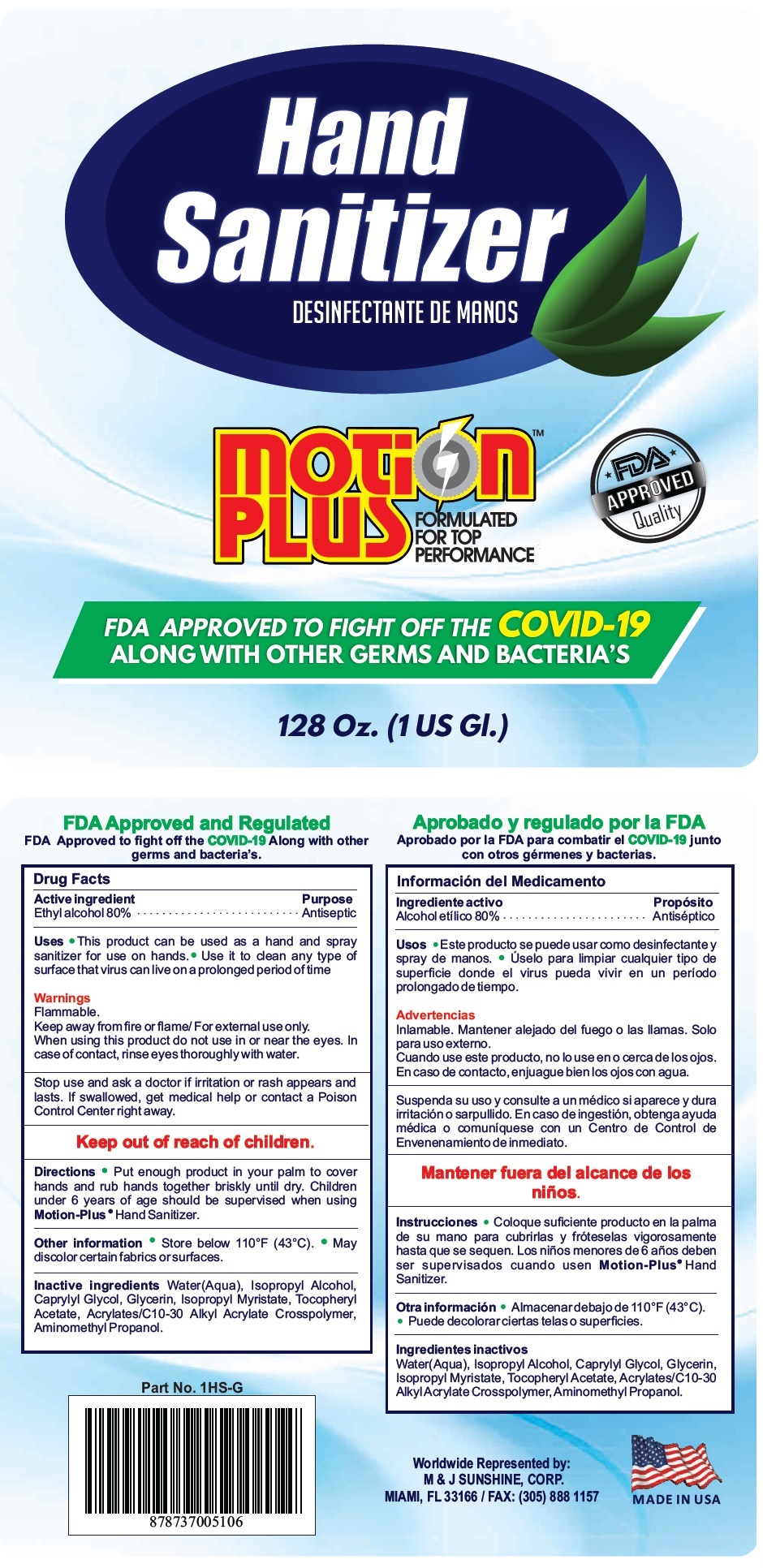 DRUG LABEL: Hand Sanitizer Motion PLUS
NDC: 77783-001 | Form: LIQUID
Manufacturer: M & J Sunshine, Corp.
Category: otc | Type: HUMAN OTC DRUG LABEL
Date: 20200610

ACTIVE INGREDIENTS: ALCOHOL 80 mL/100 mL
INACTIVE INGREDIENTS: WATER; ISOPROPYL ALCOHOL; CAPRYLYL GLYCOL; GLYCERIN; ISOPROPYL MYRISTATE; .ALPHA.-TOCOPHEROL ACETATE; CARBOMER INTERPOLYMER TYPE A (ALLYL SUCROSE CROSSLINKED); AMINOMETHYLPROPANOL

MOTiOn PLUSTM Hand Sanitizer

Active ingredient

Ethyl alcohol 80%

Purpose

Antiseptic

INDICATIONS AND USAGE

Uses • This product can be used as a hand and spray sanitizer for use on hands. • Use it to clean any type of surface that virus can live on a

prolonged period of time

Warnings

Flammable.

Keep away from fire or flame/ For external use only.

When using this product do not use in or near the eyes. In case of contact, rinse eyes thoroughly with water.

Stop use and ask a doctor if irritation or rash appears and lasts. If swallowed, get medical help or contact a Poison Control Center right away.

Keep out of reach of children.

DOSAGE AND ADMINISTRATION

Directions • Put enough product in your palm to cover hands and rub hands together briskly until dry. Children under 6 years of age

should be supervised when using Motion-Plus• Hand Sanitizer.

Other information • Store below 110°F (43°C). • May discolor certain fabrics or surfaces.

INACTIVE INGREDIENT

Inactive ingredients Water(Aqua), Isopropyl Alcohol, Caprylyl Glycol, Glycerin, Isopropyl Myristate, Tocopheryl Acetate,

Acrylates/C10-30 Alkyl Acrylate Crosspolymer, Aminomethyl Propanol.

DESINFECTANTE DE MANOS

FORMULATED FOR TOP PERFORMANCE

FDA APPROVED Quality

FDA APPROVED TO FIGHT OFF THE COVID-19

ALONG WITH OTHER GERMS AND BACTERIA'S

FDA Approved and Regulated

Worldwide Represented by:

M & J SUNSHINE, CORP.

MIAMI, FL 33166 / FAX: (305) 888 1157

MADE IN USA